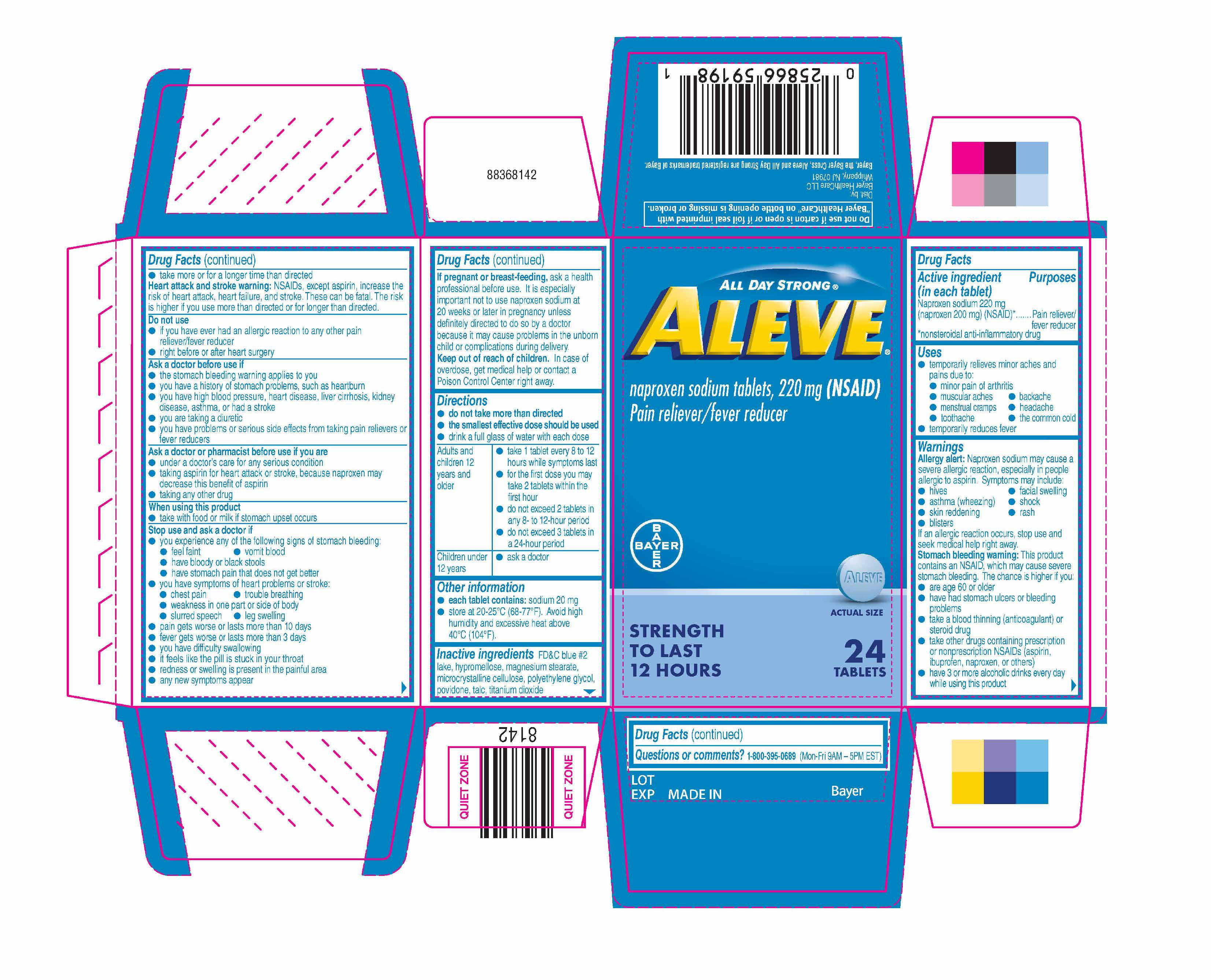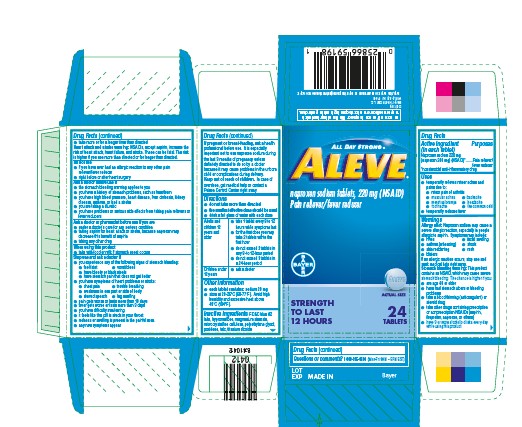 DRUG LABEL: Aleve
NDC: 0280-6010 | Form: TABLET
Manufacturer: Bayer HealthCare LLC.
Category: otc | Type: HUMAN OTC DRUG LABEL
Date: 20251204

ACTIVE INGREDIENTS: NAPROXEN SODIUM 220 mg/1 1
INACTIVE INGREDIENTS: CELLULOSE, MICROCRYSTALLINE; POLYETHYLENE GLYCOL, UNSPECIFIED; POVIDONE; TALC; TITANIUM DIOXIDE; FD&C BLUE NO. 2; HYPROMELLOSES; MAGNESIUM STEARATE

Aleve® Tablets UI 1600169

Drug Facts

Active ingredient (in each tablet)

Naproxen sodium 220 mg (naproxen 200 mg) (NSAID) [nonsteroidal anti-inflammatory drug]

Purposes

Pain reliever/fever reducer

Uses

- temporarily relieves minor aches and pains due to:
  - minor pain of arthritis
  - muscular aches
  - backache
  - menstrual cramps
  - headache
  - toothache
  - the common cold
- temporarily reduces fever

Directions

- do not take more than directed
- the smallest effective dose should be used
- drink a full glass of water with each dose

- Adults and children 12 years and older | - take 1 tablet every 8 to 12 hours while symptoms last - for the first dose you may take 2 tablets within the first hour - do not exceed 2 tablets in any 8- to 12-hour period - do not exceed 3 tablets in a 24-hour period
- Children under 12 years | - ask a doctor

Other information

- each tablet contains: sodium 20 mg
- store at 20-25ºC (68-77ºF). Avoid high humidity and excessive heat above 40°C (104°F).

Inactive ingredients

FD&C blue #2 lake, hypromellose, magnesium stearate, microcrystalline cellulose, polyethylene glycol, povidone, talc, titanium dioxide

Questions or comments?

1-800-395-0689 (Mon-Fri 9AM – 5PM EST)

Dist. by:
Bayer HealthCare LLC
Whippany, NJ 07981

KEEP OUT OF REACH OF CHILDREN

In case of overdose, get medical help or contact a Poison Control Center right away.

PRINCIPAL DISPLAY PANEL - 24 Tablet Bottle Carton

ALL DAY STRONG®
ALEVE®
naproxen sodium tablets, 220 mg (NSAID)
Pain reliever/fever reducer

STRENGTH TO LAST 12 HOURS

ACTUAL SIZE
24 TABLETS